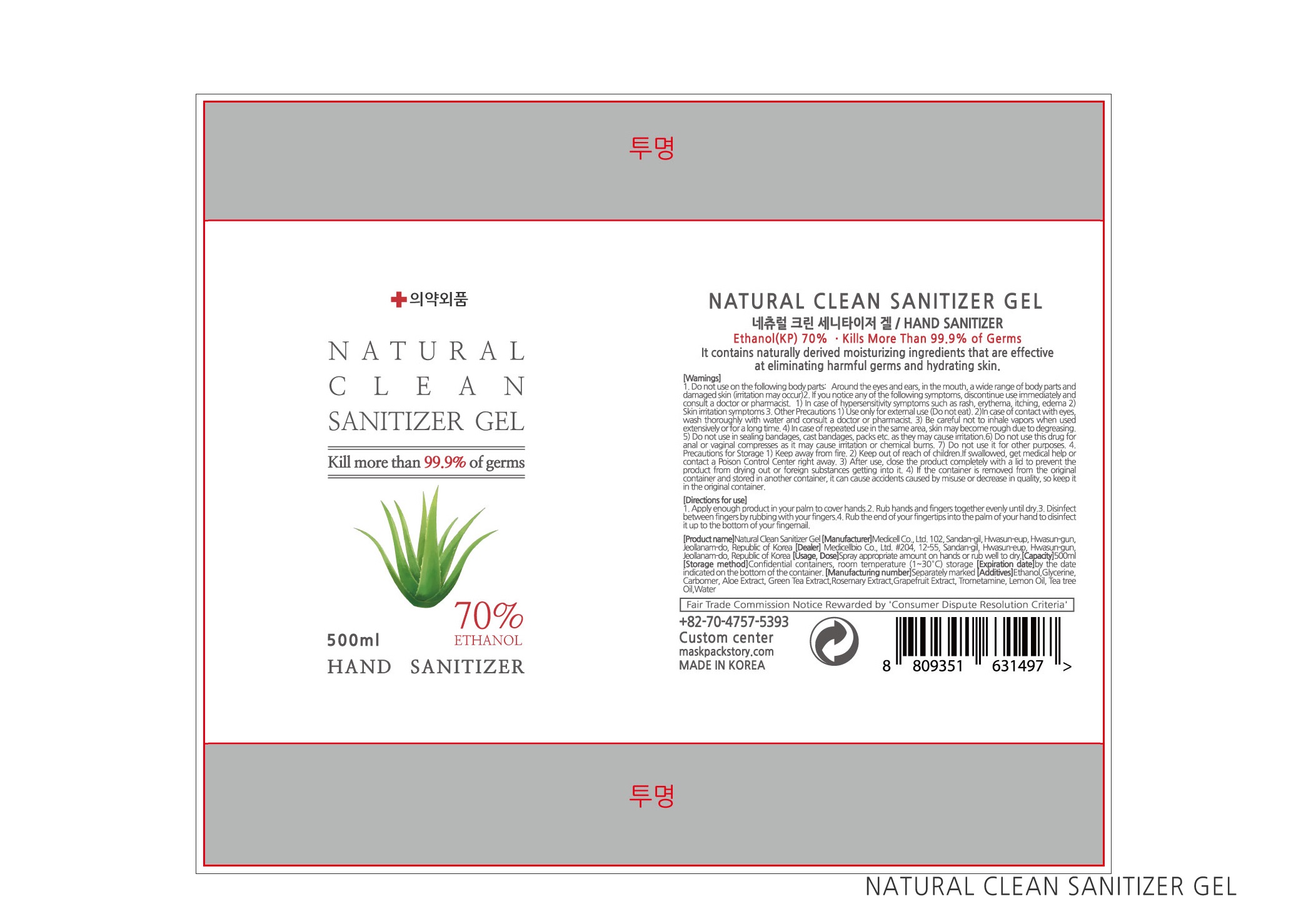 DRUG LABEL: Natural Clean Sanitizer gel
NDC: 75332-0009 | Form: GEL
Manufacturer: MEDICELL CO.,LTD
Category: otc | Type: HUMAN OTC DRUG LABEL
Date: 20200704

ACTIVE INGREDIENTS: ALCOHOL 70 mL/100 mL
INACTIVE INGREDIENTS: GREEN TEA LEAF; GLYCERIN; GRAPEFRUIT PEEL; ROSEMARY OIL; LEMON OIL; ALOE VERA LEAF; CARBOMER 940; TROLAMINE; WATER

Drug Facts

ACTIVE INGREDIENT

alcohol

INACTIVE INGREDIENT

Water
Glycerin
Carbomer
Aloe Extract
Green Tea Extract
Rosemary Extract
Grapefruit Extract
Tromethamine
Tea tree oil
Lemon Oil

PURPOSE

Sterilization of hands and skin

KEEP OUT OF REACH OF THE CHILDREN

INDICATIONS AND USAGE

Apply to clean, dry hands. Apply sufficient amount to thoroughly wet all surfaces of hands and fingers. Rub onto hands until dry.

WARNINGS

■ Flammable. Keep away from fire or flame.

■ For external use only.

■ Do not use in eyes.

■ lf swallowed, get medical help promptly.

■ Stop use, ask doctor lf irritation occurs.

■ Keep out of reach of children.

DOSAGE AND ADMINISTRATION

for external use only